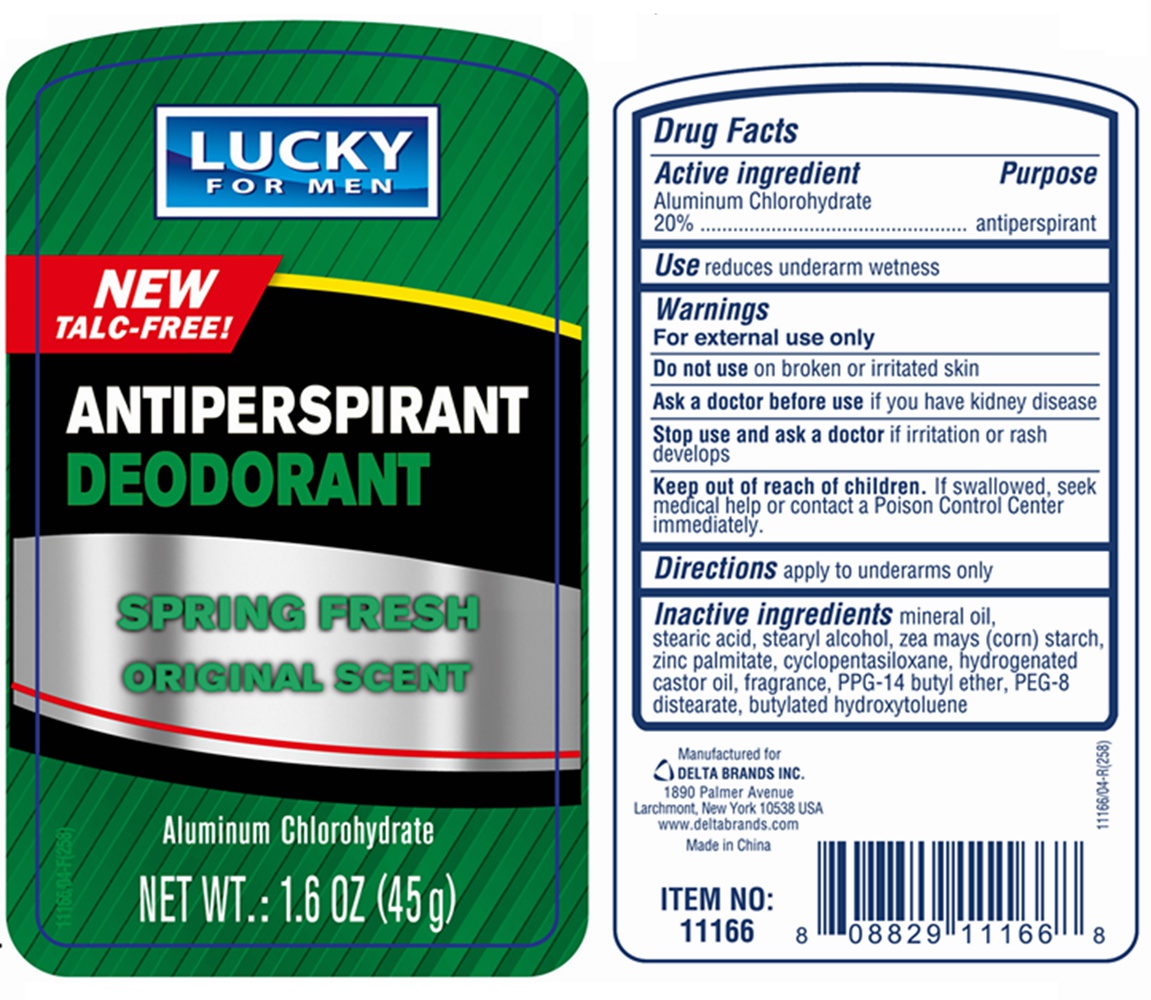 DRUG LABEL: LUCKY ANTIPERSPIRANT DEODORANT SPRING FRESH
NDC: 76176-011 | Form: STICK
Manufacturer: Ningbo Liyuan Daily Chemical Products Co., Ltd.
Category: otc | Type: HUMAN OTC DRUG LABEL
Date: 20240101

ACTIVE INGREDIENTS: ALUMINUM CHLOROHYDRATE 20 g/100 g
INACTIVE INGREDIENTS: STEARIC ACID; HYDROGENATED CASTOR OIL; STEARYL ALCOHOL; MINERAL OIL; CYCLOMETHICONE 5; PEG-8 DISTEARATE; BUTYLATED HYDROXYTOLUENE; ZINC PALMITATE; PPG-14 BUTYL ETHER

Active ingredient

Aluminum Chlorohydrate 20%

Purpose

antiperspirant

Use

reduces underarm wetness

Warnings

For external use only

Do not use

on broken or irritated skin

Ask a doctor before use

if you have kidney disease

Stop use and ask a doctor

if irritation or rash develops

Keep out of reach of children.

If swallowed, seek medical help or contact a Poison Control Center immediately.

Directions

apply to underarms only

Inactive ingredients

mineral oil, stearic acid, stearyl alcohol, zea mays (corn) starch, zinc palmitate, cyclopentasiloxane, hydrogenated castor oil, fragrance, PPG-14 butyl ether, PEG-8 distearate, butylated hydroxytoluene